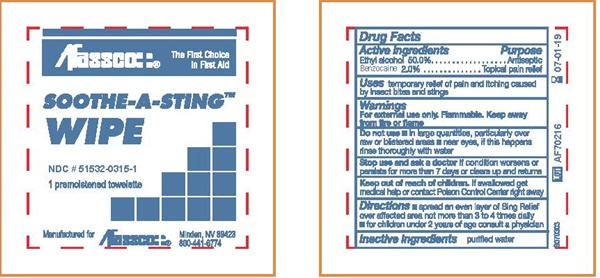 DRUG LABEL: SOOTHE-A-STING
NDC: 51532-0315 | Form: LIQUID
Manufacturer: Afassco Inc
Category: otc | Type: HUMAN OTC DRUG LABEL
Date: 20191223

ACTIVE INGREDIENTS: ALCOHOL 0.4 g/1 mL; BENZOCAINE 0.02 g/1 mL
INACTIVE INGREDIENTS: WATER

Soothe-A-Sting - 0315

Drug Facts Active Ingredients

Ethyl alcohol 50.0%

Benzocaine 2.0%

Purpose

Antiseptic

Topcal pain relief

Keep out of reach of children. If swallowed, get medical help or contact a Poison Control Center right away.

Uses

temporary relief of pain and itching caused by insect bites and stings

Do not use

- in large quantites, particularly over raw or blistered areas
- near eyes, if this happens rinse thoroughly with water

Warnings

For external use only. Flammable. Keep away from fire or flame.

Stop use and ask a doctor if

condition worsens or persists for more than 7 days or clears up and returns

Directions

- spread an even layer of Sting Relief over affected area not mor than 3 to 4 times daily.
- for children under 2 years of age consult a physician

Inactive ingredients

purified water

SOOTHE-A-STING product label

Afassco: The First Choice In First Aid

SOOTHE-A-STING™ WIPE

NDC # 51532-0315-1

1 premoistened towlette

Manufactured for Afassco::® Minden, NV 89423

800-441-6774

LOT AF70216

EXP 07-01-19

res